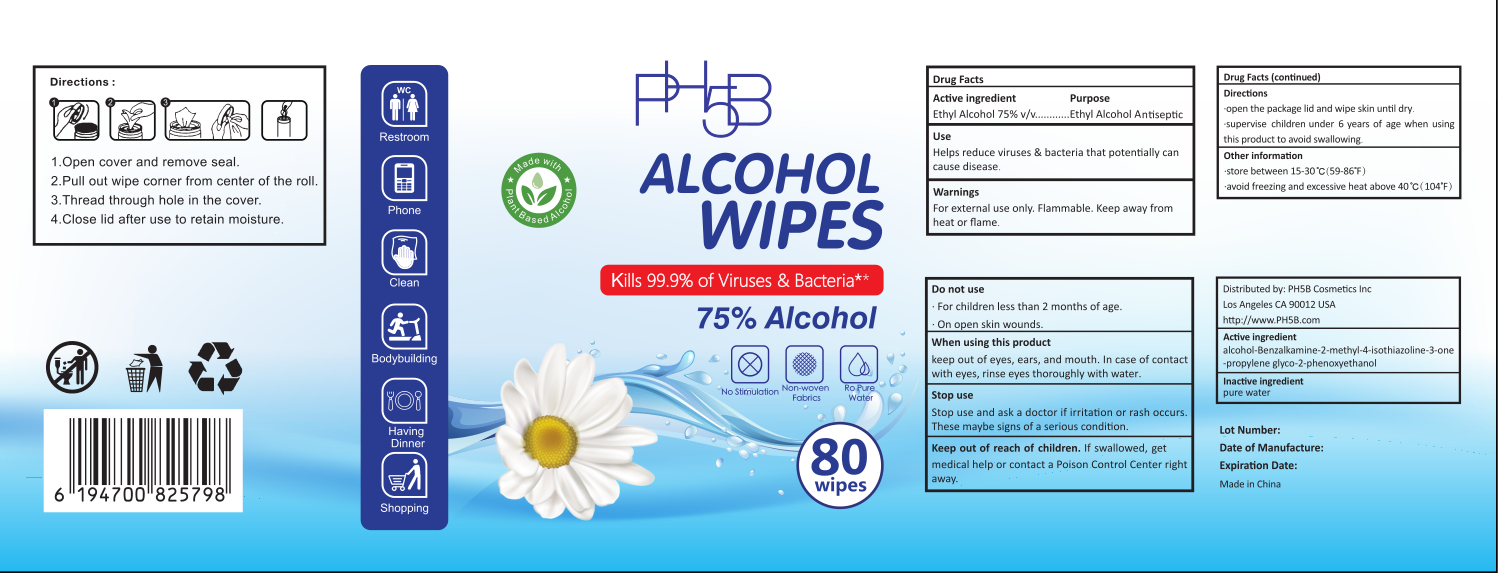 DRUG LABEL: Alcohol disinfectant wipes
NDC: 41546-018 | Form: CLOTH
Manufacturer: Zhejiang Huanghua Biological Technology Co., Ltd
Category: otc | Type: HUMAN OTC DRUG LABEL
Date: 20201207

ACTIVE INGREDIENTS: ALCOHOL 315 mL/80 1; BENZALKONIUM CHLORIDE 7.4 g/80 1; METHYLISOTHIAZOLINONE 7.4 g/80 1; PROPYLENE GLYCOL 7.4 g/80 1; PHENOXYETHANOL 7.4 g/80 1
INACTIVE INGREDIENTS: WATER

DOSAGE AND ADMINISTRATION

store between 15-30°C(59-86°F)
avoid freezing and excessive heat above 40°C(104°F)

INACTIVE INGREDIENT

pure water

INDICATIONS AND USAGE

1.Open cover and remove seal.
2.Pull out wipe corner from center of the roll.
3.Thread through hole in the cover.
4.Close lid after use to retain moisture.

ACTIVE INGREDIENT

alcohol

Benzalkamine

2-methyl-4-isothiazoline-3-one

propylene glyco

2-phenoxyethanol

DO NOT USE

For children less than 2 months of age.
On open skin wounds.

keep out of reach of children

PURPOSE

Disinfection
Sterilization
No Rinseing

WARNINGS

For external use only. Flammable. Keep away from heat or flame.